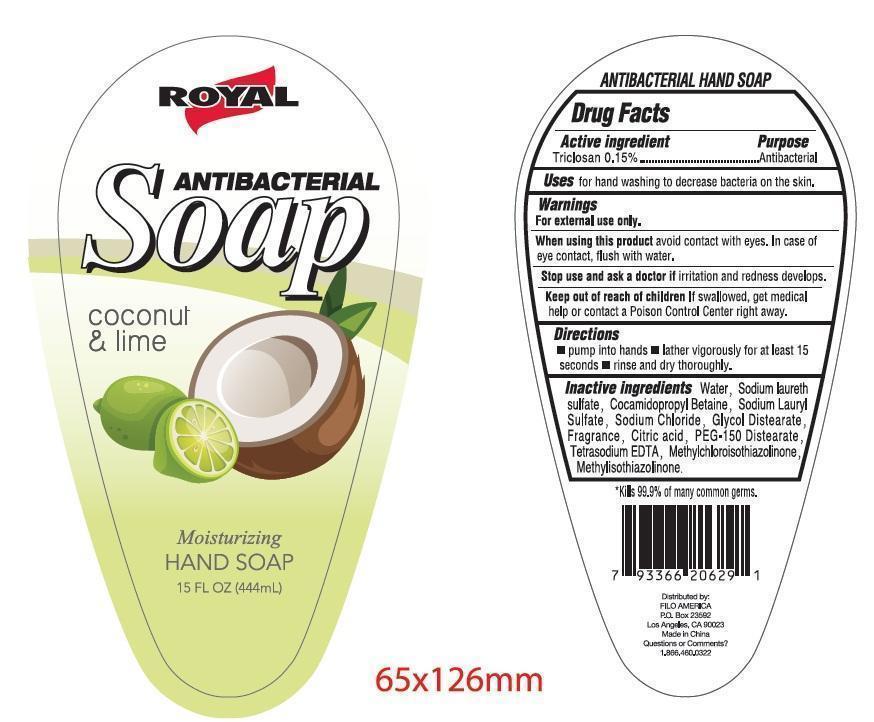 DRUG LABEL: Royal Antibacterial (coconut and lime) moisturizing hand cleanse
NDC: 50438-603 | Form: GEL
Manufacturer: Filo America
Category: otc | Type: HUMAN OTC DRUG LABEL
Date: 20150605

ACTIVE INGREDIENTS: TRICLOSAN 1.5 mg/1 mL
INACTIVE INGREDIENTS: WATER; SODIUM LAURETH SULFATE; COCAMIDOPROPYL BETAINE; SODIUM LAURYL SULFATE; SODIUM CHLORIDE; PEG-150 DISTEARATE; CITRIC ACID MONOHYDRATE; EDETATE DISODIUM; METHYLCHLOROISOTHIAZOLINONE; METHYLISOTHIAZOLINONE; FD&C YELLOW NO. 5; FD&C BLUE NO. 1

Active Ingredient

Triclosan 0.15%

Purpose

Antibacterial

Uses

for handwashing to decrease bacteria on the skin.

Warnings

For external use only.

When using this product

Avoid contact with eyes. In case of eye contact, flush with water.

Stop use and ask a doctor

If irritation and redness develops.

Keep out of reach of children.

If swallowed, get medical help or contact a Poison Control Center right away.

Directions

- pump into hands
- lather vigorously for at least 15 seconds
- rinse and dry thoroughly.

Inactive Ingredients

Water, Sodium Laureth Sulfate, Cocamidopropyl Betaine, Sodium Lauryl Sulfate, Sodium Chloride, Fragrance, Citric Acid, Peg-150 Distearate, Tetrasodium Edta, FD&C Yellow No.5, FD&C Blue No.1